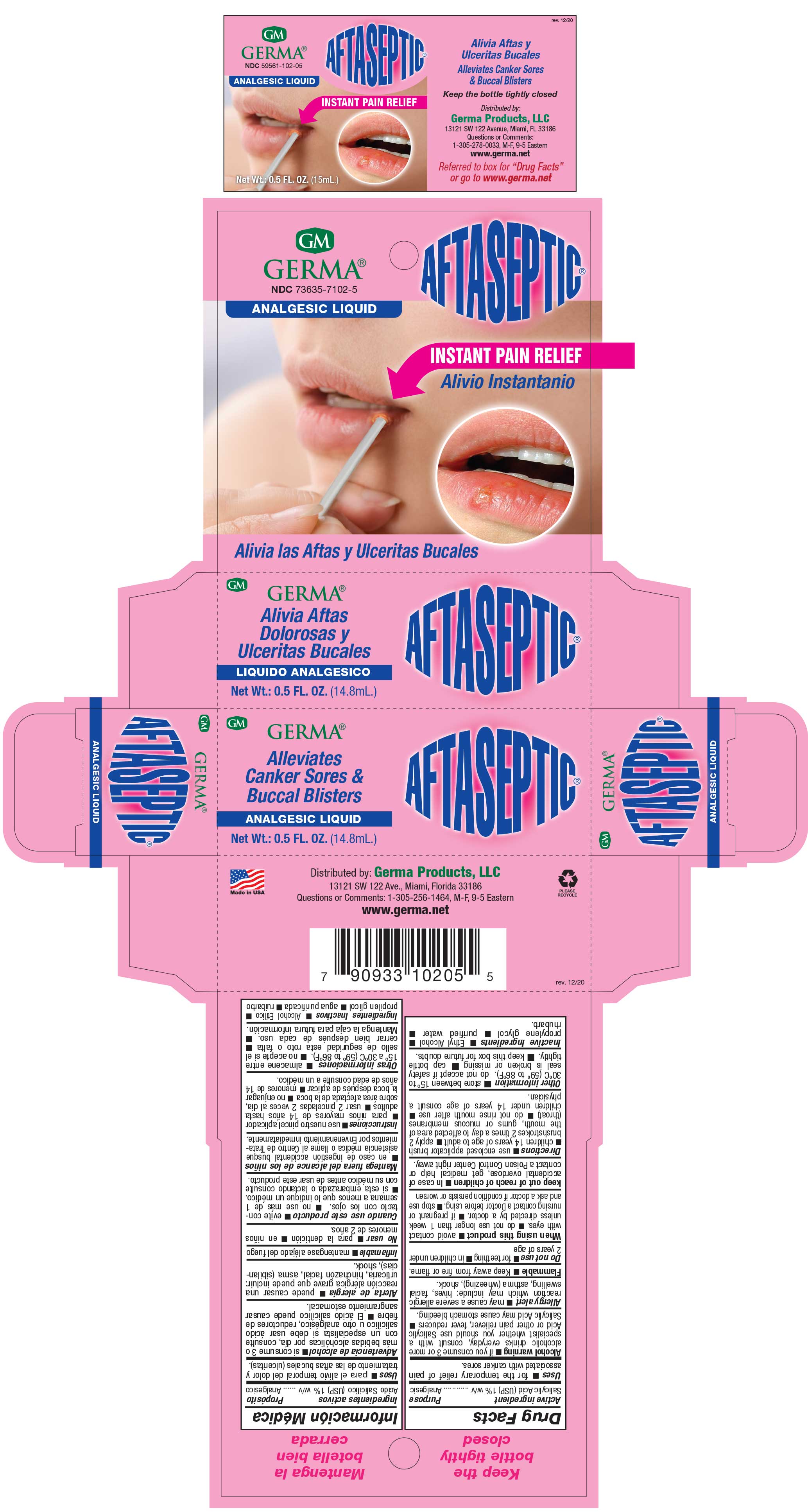 DRUG LABEL: Aftaseptic
NDC: 73635-7102 | Form: LIQUID
Manufacturer: Germa Products, LLC
Category: otc | Type: HUMAN OTC DRUG LABEL
Date: 20251010

ACTIVE INGREDIENTS: SALICYLIC ACID 10 mg/1 mL
INACTIVE INGREDIENTS: PROPYLENE GLYCOL; ALCOHOL; RHUBARB

Aftaseptic Analgesic Liquid

Active Ingredient

Salicylic Acid 1% w/v

Purpose

Analgesic

Uses

For the temporary relief of pain associated with canker sores.

INDICATIONS AND USAGE

for the temporary relief of pain associated with canker sores.

Warnings

Alcohol warning: if you consume 3 or more alcoholic drinks everyday, consult with a specialist whether you should use Salicylic Acid or other pain reliever, fever reducers n Salicylic Acid may cause stomach bleeding.

Allergy alert: may cause a severe allergic reaction which may include: hives, facial swelling, asthma (wheezing), shock.

Warnings

Flammable n Keep away from fire or flame. Do not use for teething or in children under 2 years of age
When using this product n avoid contact with eyes. Do not use longer than 1 week unless directed by a doctor. If pregnant or nursing contact a Doctor before using. Stop use and ask a doctor if condition persists or worsen
keep out of reach of children. In case of accidental overdose, get medical help or contact a Poison Control Center right away.

Other Information

Store between 15º to 30ºC (59º to 86ºF). Cap bottle tightly. Do not accept if safety seal is broken or missing. Cap bottle tightly. Keep this box for future doubts.

Directions

Use enclosed applicator brush

Children 14 years of age to adult. Apply 2 brushstrokes 2 times a day to affected area of the mouth, gums or mucous membranes (throat). Do not rinse mouth after use. Children under 14 years of age consult a physician.

Inactive Ingredients

Ethyl Alcohol, propylene glycol, purified water, rhubarb.

PACKAGE LABEL

Aftaseptic